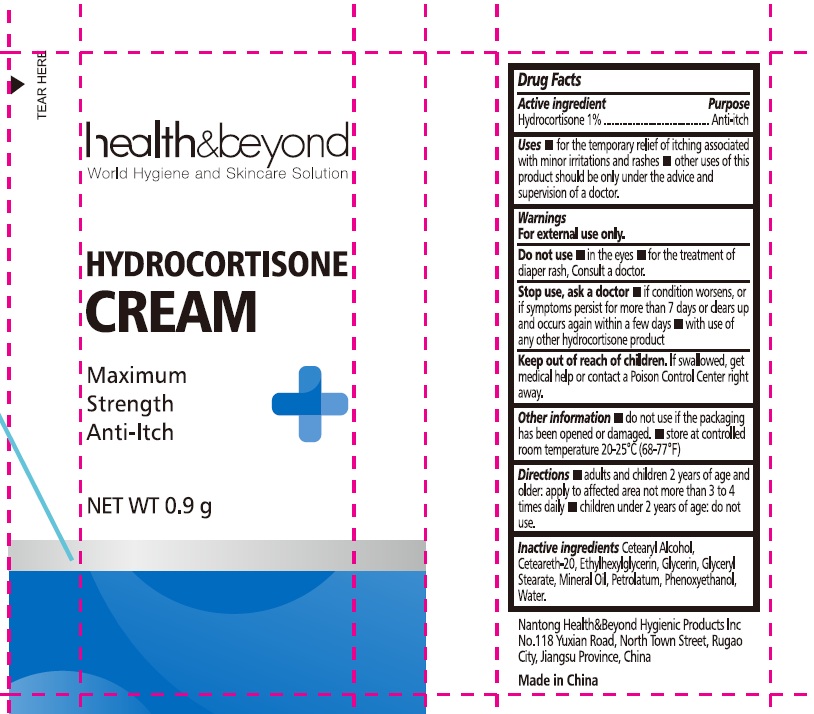 DRUG LABEL: health beyond
NDC: 43473-092 | Form: CREAM
Manufacturer: Nantong Health & Beyond Hygienic Products Inc.
Category: otc | Type: HUMAN OTC DRUG LABEL
Date: 20251123

ACTIVE INGREDIENTS: HYDROCORTISONE 1 g/100 g
INACTIVE INGREDIENTS: GLYCERIN; POLYOXYL 20 CETOSTEARYL ETHER; CETOSTEARYL ALCOHOL; ETHYLHEXYLGLYCERIN; WATER; MINERAL OIL; PETROLATUM; PHENOXYETHANOL; GLYCERYL STEARATE SE

43473-092 health and beyond Hydrocortison Cream

Active ingredient

Hydrocortisone 1%

Purpose Anti-itch

Uses

- for temorary relief of itching associated with minor irritations and rashes
- other uses of this product should be only under the advice and supervision of a doctor

Warnings

For external use only.

Do not use

- for the treatment of diaper rash. Consult a doctor

Stop use and ask a doctor

- if condition worsens, or if symptoms persist for more than 7 days, or clears up and occurs again within a few days
- with use of any other hydrocortisone products

Keep out of reach of children. If swallowed, get medical help or contact a Poison Control Center right away.

Other Information

- Do not use if the packaging has been opened or damaged
- Store at controlled room temperature 20-25C (68-77F)

Directions

- adults and children 2 years of age and older: apply to affected area not more than 3 to 4 times daily
- children under 2 years of age: do not use

Inactive ingredients

cetearyl alcohol, ceteareth-20, ethylhexylglycerin, glycerin, glyceryl stearate, mineral oil, petrolactum, phenoxyethanol, water